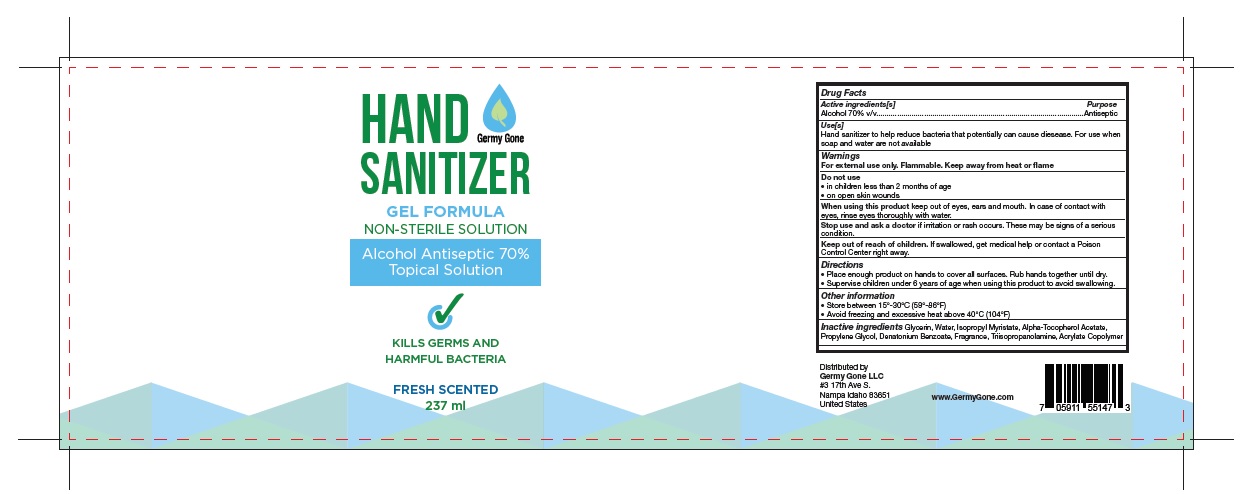 DRUG LABEL: Germy Gone Hand Sanitizer
NDC: 79725-001 | Form: GEL
Manufacturer: GERMY GONE LLC
Category: otc | Type: HUMAN OTC DRUG LABEL
Date: 20200709

ACTIVE INGREDIENTS: ALCOHOL 70 mL/100 mL
INACTIVE INGREDIENTS: WATER; .ALPHA.-TOCOPHEROL ACETATE; DENATONIUM BENZOATE; GLYCERIN; ISOPROPYL MYRISTATE; PROPYLENE GLYCOL; METHACRYLIC ACID - ETHYL ACRYLATE COPOLYMER (4500 MPA.S); TRIISOPROPANOLAMINE; LINALOOL, (+)-; FRAGRANCE LAVENDER & CHIA F-153480; CUMINYL ACETALDEHYDE

Active Ingredient

Alcohol 70% v/v.

Purpose

Antiseptic

Use

Hand Sanitizer to help reduce bacteria that potentially can cause disease. For use when soap and water are not available.

Warnings

For external use only. Flammable. Keep away from heat or flame.

Do not use

- in children less than 2 months of age
- on open skin wounds

When using this product keep out of eyes, ears, and mouth. In case of contact with eyes, rinse eyes thoroughly with water.

Stop use and ask a doctor if irritation or rash occurs. These may be signs of a serious condition.

Keep out of reach of children. If swallowed, get medical help or contact a Poison Control Center right away.

Directions

- Place enough product on hands to cover all surfaces. Rub hands together until dry.
- Supervise children under 6 years of age when using this product to avoid swallowing.

Other information

- Store between 15o-30oC (59o-86oF)
- Avoid freezing and excessive heat above 40oC (104oF)

Inactive ingredients

glycerin, isopropyl myristate, methacrylic acid, propylene glycol, purified water USP, tetrahydroxypropyl ethylenediamine, vitamin E